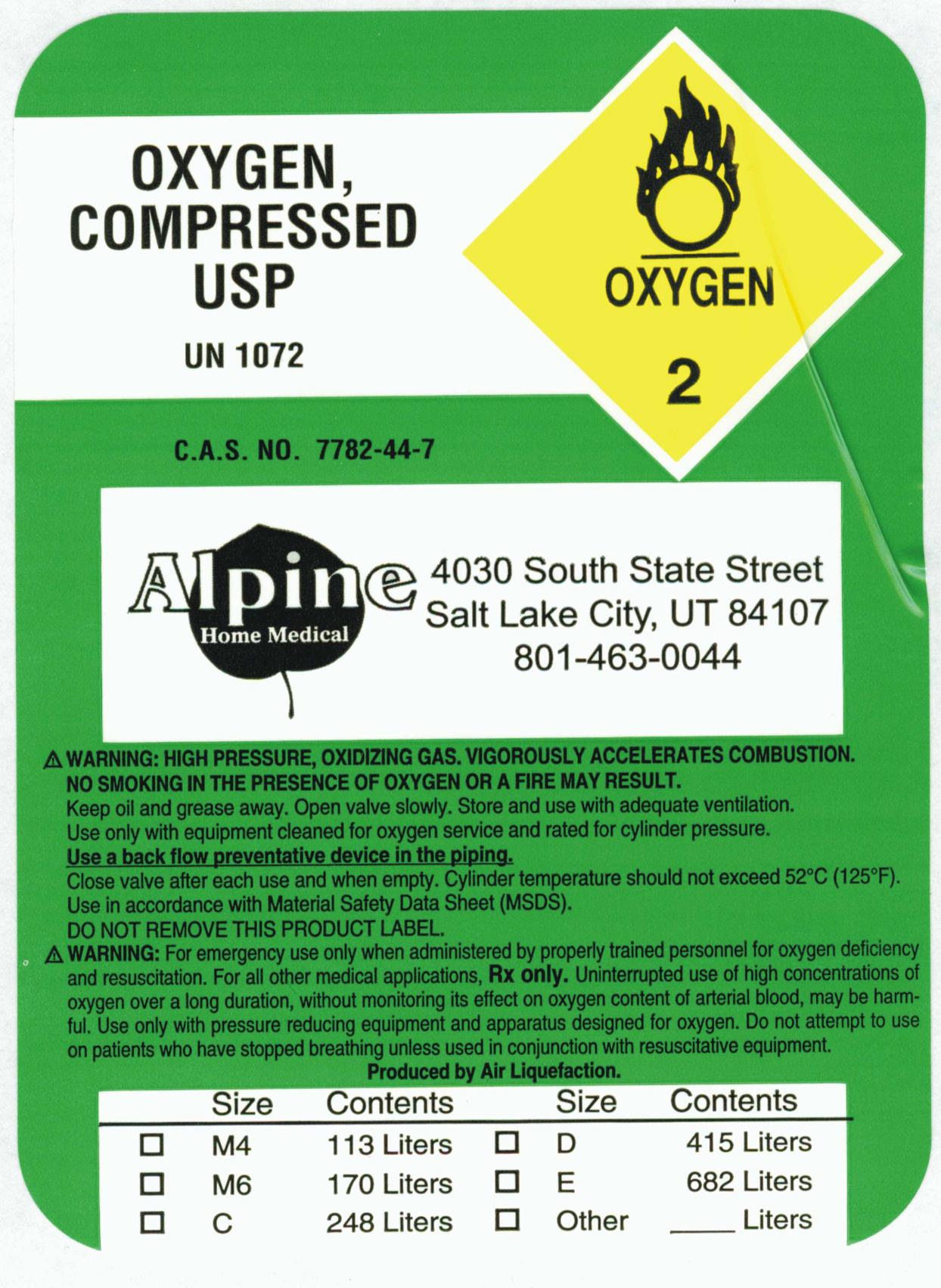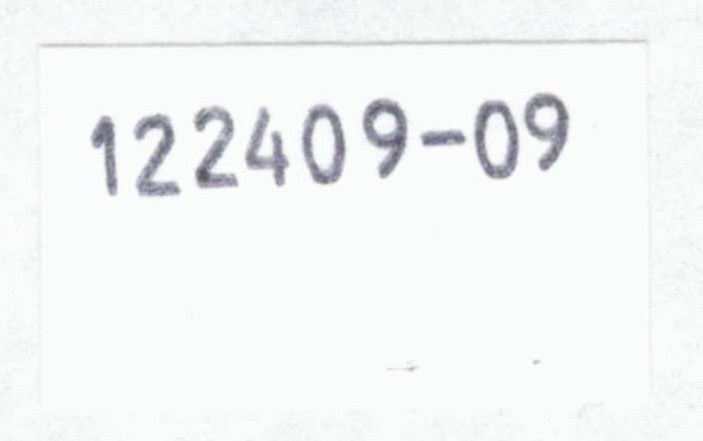 DRUG LABEL: Oxygen
NDC: 66552-0001 | Form: GAS
Manufacturer: Alpine Home Medical Equipment
Category: prescription | Type: HUMAN PRESCRIPTION DRUG LABEL
Date: 20091228

ACTIVE INGREDIENTS: Oxygen 99 L/100 L

Oxygen